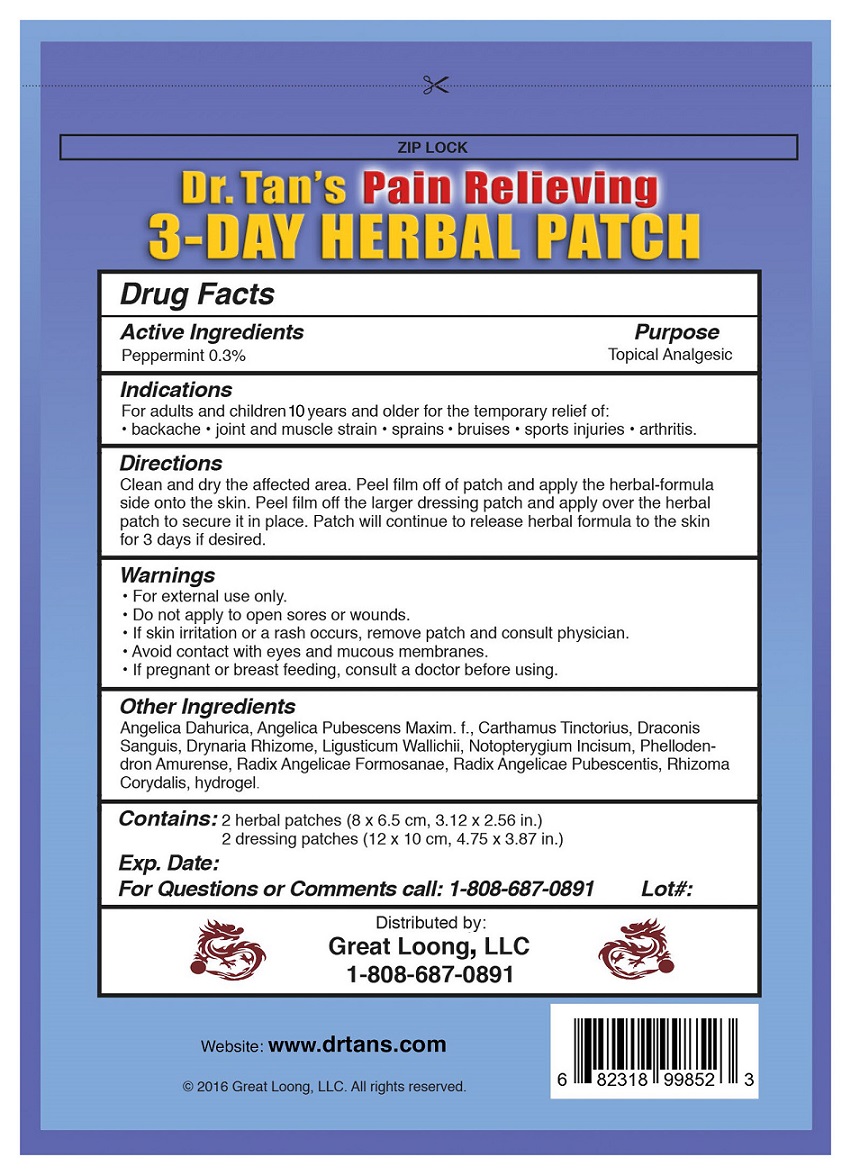 DRUG LABEL: Dr Tans Pain Releiving 3 day Herabl Patch
NDC: 71446-002 | Form: PATCH
Manufacturer: Great Loong LLC
Category: otc | Type: HUMAN OTC DRUG LABEL
Date: 20220113

ACTIVE INGREDIENTS: PEPPERMINT OIL 0.3 g/1 g
INACTIVE INGREDIENTS: ANGELICA PUBESCENS ROOT; CARTHAMUS TINCTORIUS FLOWER BUD; DRAGON'S BLOOD; DRYNARIA FORTUNEI ROOT; LIGUSTICUM WALLICHII ROOT; NOTOPTERYGIUM INCISUM ROOT; PHELLODENDRON AMURENSE BARK; ANGELICA DAHURICA VAR. FORMOSANA ROOT; DICENTRA CANADENSIS ROOT; GLYCERIN; CROSPOVIDONE; POVIDONE K90; SODIUM POLYACRYLATE (8000 MW); SODIUM BENZOATE

Dr Tan's Pain-Releiving 3 day Patch

Actives

PEPPERMINT 0.3 %

Inactives

Angelica Dahurica, Angelica Pubescens Maxim. f. , Carthamus Tinctorius, Draconis Sanguis, Drynaria Rhizome, Ligusticum Wallichii, Notopterygium lncisum, Phellodendron Amurense, Radix Angelicae Formosanae, Radix Angelicae Pubescentis, Rhizoma Corydalis, hydrogel.

Purpose

External Analgesic

Indication and Usage

For adults and children 10 and older for the temporary relief of: • chronic arthritis • backache • joint and muscle pain and stiffness • old sports injuries.

Directions

Clean and dry the affected area. Peel film off of patch and apply the herbal-formula side onto the skin. Peel film off the larger dressing patch and apply over the herbal patch to secure it in place. Patch will continue to release herbal formula to the skin for 3 days if desired.

Warnings

• For external use only. • Do not apply to open sores or wounds. • If skin irritation or a rash occurs, remove patch and consult physician. ·Avoid contact with eyes and mucous membranes. • If pregnant or breast feeding, consult a doctor before using.

Keep out of reach of children